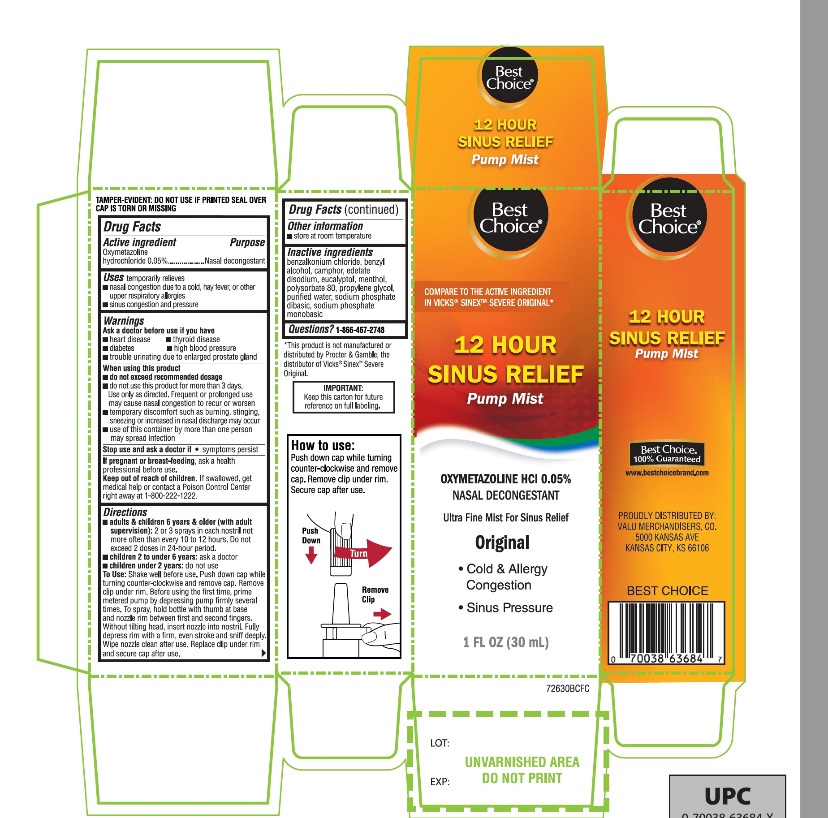 DRUG LABEL: Best Choice

NDC: 63941-726 | Form: SPRAY
Manufacturer: BEST CHOICE (VALU MERCHANDISERS COMPANY)
Category: otc | Type: HUMAN OTC DRUG LABEL
Date: 20250717

ACTIVE INGREDIENTS: OXYMETAZOLINE HYDROCHLORIDE 0.05 g/100 mL
INACTIVE INGREDIENTS: BENZALKONIUM CHLORIDE; BENZYL ALCOHOL; CAMPHOR (NATURAL); EDETATE DISODIUM; EUCALYPTOL; MENTHOL, UNSPECIFIED FORM; POLYSORBATE 80; PROPYLENE GLYCOL; WATER; SODIUM PHOSPHATE, DIBASIC, UNSPECIFIED FORM; SODIUM PHOSPHATE, MONOBASIC, UNSPECIFIED FORM

Best Choice Sinus Relief Drug Facts

Active ingredient

Oxymetazoline hydrochloride 0.05%

Purpose

Nasal Decongestant

Uses

temporarily relieves

- nasal congestion due to a cold, heavy fever, or other upper respiratory allergies
- Sinus congestion and pressure

Ask a doctor before use if you have

- heart disease
- high blood pressure
- diabetes
- thyroid disease
- trouble urinating due to an enlarged prostate gland

When using this product

- do not exceed recommended dosage
- do not use this product for more than 3 days. Use only as directed. Frequent or prolonged use may cause nasal congestion to recur or worsen.
- temporary discomfort such as burning, stinging, sneezing or an increase in nasal discharge may occur
- use of this container by more than one person may spread infection

Stop use and ask a doctor if

- symptoms persist

If pregnant or breast-feeding,

ask a health professional before use.

Keep out of reach of children.

If swallowed, get medical help or contact a Poison Control Center right away at (1-800-222-1222).

Directions

- adults & children 6 years & older (with adult supervision):2 or 3 sprays in each nostril not more often than every 10 to 12 hours. Do not exceed 2 doses in any 24-hour period.
- Children 2 to under 6 years:ask a doctor
- Children 2 years:ask a doctor

Shake well before use.Before using the first time, remove the protective cap from the tip by pressing and twisting off the cap. Rotate the lock tab to align arrow marks to unlock the pump. Prime metered pump by depressing pump firmly several times. To spray, hold bottle with thumb at base and nozzle between first and second fingers without titling head, insert nozzle into nostril. Fully depress rim with a firm, even stroke and sniff deeply. Wipe nozzle clean after use. Lock the pump by ensuring that arrow marks are not aligned and replace the protective cap on tip.

Other information

- store at room temperature

Inactive ingredients

benzalkonium chloride, benzyl alcohol, camphor, edetate disodium, eucalyptol, menthol, polysorbate 80, propylene glycol, purified water, sodium phosphate dibasic, sodium phosphate monobasic.

Questions or comments?

1-866-467-2748

Principal Display Panel

Best Choice®

NDC# 63941-726-30

COMPARE TO THE ACTIVE INGREDIENT IN VICKS® SINEX®*

12 HOUR SINUS RELIEF

OXYMETAZOLINE HCl 0.05%

NASAL DECONGESTANT

Ultra-Fine Mist For Sinus Relief

- Cold & allergy congestion
- Sinus pressure

1 FL OZ (30 mL)

IMPORTANT: KEEP THE CARTON FOR FUTURE REFERENCE ON FULL LABELING

Best Choice® 100% Guaranteed

www.bestchoicebrand.com

PROUDLY DISTRIBUTED BY:

VALU MERCHANDISERS, CO.

5000 KANSAS AVE

KANSAS CITY, KS 66106

*This product is not manufactured or distributed by Procter and Gamble, the distributer of Vicks®Sinex®